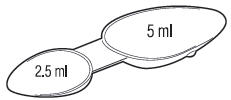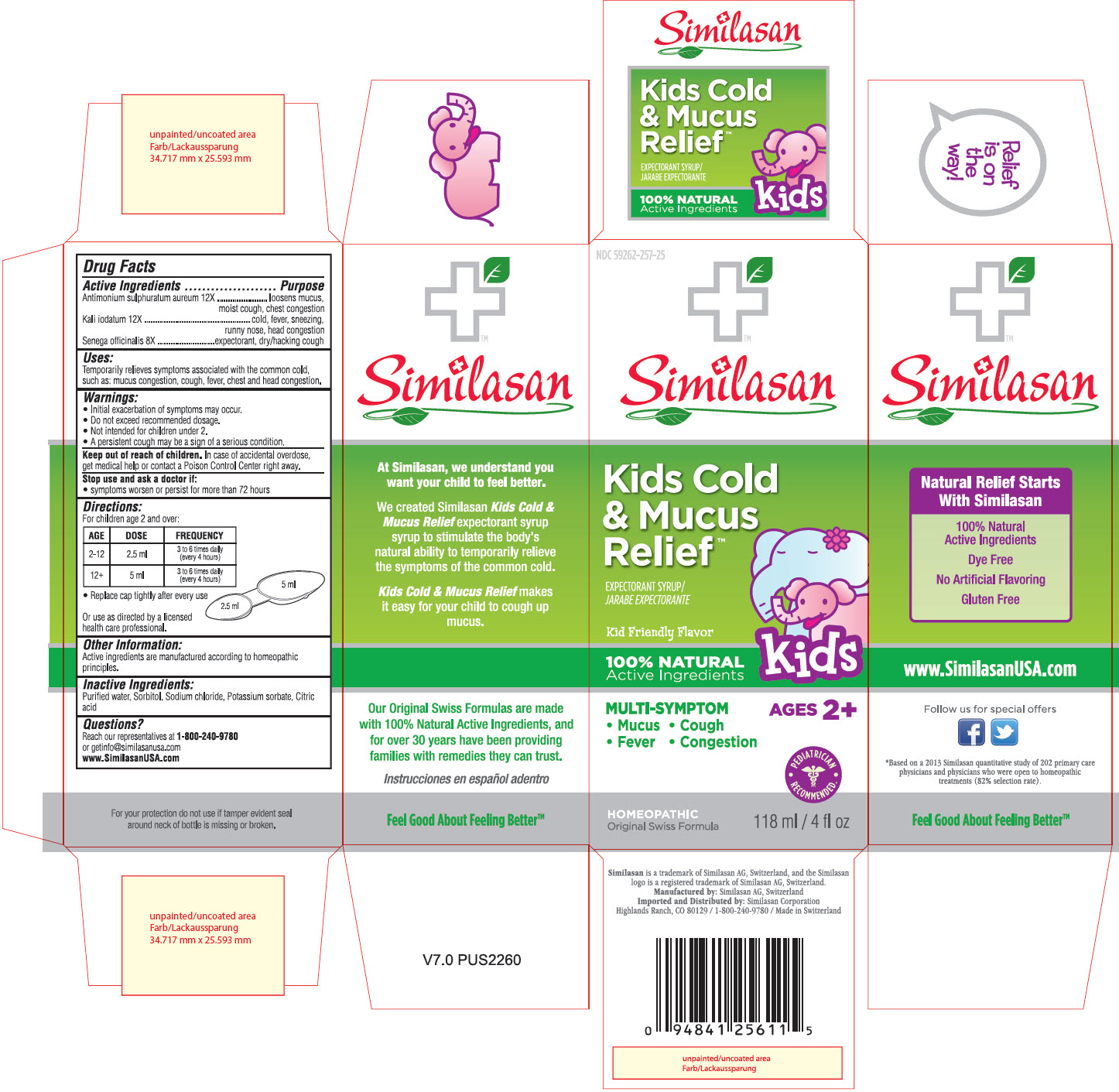 DRUG LABEL: Kids Cold and Mucus Relief Expectorant
NDC: 59262-257 | Form: SYRUP
Manufacturer: Similasan Corporation
Category: homeopathic | Type: HUMAN OTC DRUG LABEL
Date: 20130702

ACTIVE INGREDIENTS: ANTIMONY PENTASULFIDE 12 [hp_X]/118 mL; POTASSIUM IODIDE 12 [hp_X]/118 mL; POLYGALA SENEGA ROOT 8 [hp_X]/118 mL
INACTIVE INGREDIENTS: WATER; SORBITOL; POTASSIUM SORBATE; CITRIC ACID MONOHYDRATE; SODIUM CHLORIDE

Kids Cold and Mucus Relief

Active Ingredient

Antimonium sulphuratum aureum 12X

Purpose

loosens mucus, moist cough, chest congestion

Active Ingredient

Kali iodatum 12X

Purpose

cold, fever, sneezing, runny nose, head congestion

Active Ingredient

Senega offcinalis 8X

Purpose

expectorant, dry/hacking cough

Uses:

Temporarily relieves symptoms associated with the common cold, such as: mucus congestion, cough, fever, chest and head congestion.

Warnings:

- Initial exacerbation of symptoms may occur.
- Do not exceed recommended dosage.
- Not intended for children under 2.
- A persistent cough may be a sign of a serious condition.

Keep out of reach of children.

In case of accidental overdose, get medical help or contact a Poison Control Center right away.

Stop use and ask a doctor if:

- symptoms worsen or persist for more than 72 hours

Directions:

For children age 2 and over:

AGE | DOSE | FREQUENCY
2-12 | 2.5 ml | 3 to 6 times daily (every 4 hours)
12+ | 5 ml | 3 to 6 times daily (every 4 hours)

• Replace cap tightly after every use

Or use as directed by a licensed health care professional.

Other Information:

Active ingredients are manufactured according to homeopathic principles.

Inactive Ingredients:

Purified water, Sorbitol, Sodium chloride, Potassium sorbate, Citric acid

Questions?

Reach our representatives at 1-800-240-9780 or getinfo@similasanusa.com
www.SimilasanUSA.com

PRINCIPAL DISPLAY PANEL

NDC 59262-257-25
Similasan
Kids Cold & Mucus Relief
EXPECTORANT SYRUP/
JARABE EXPECTORANTE
118 ml / 4 fl oz